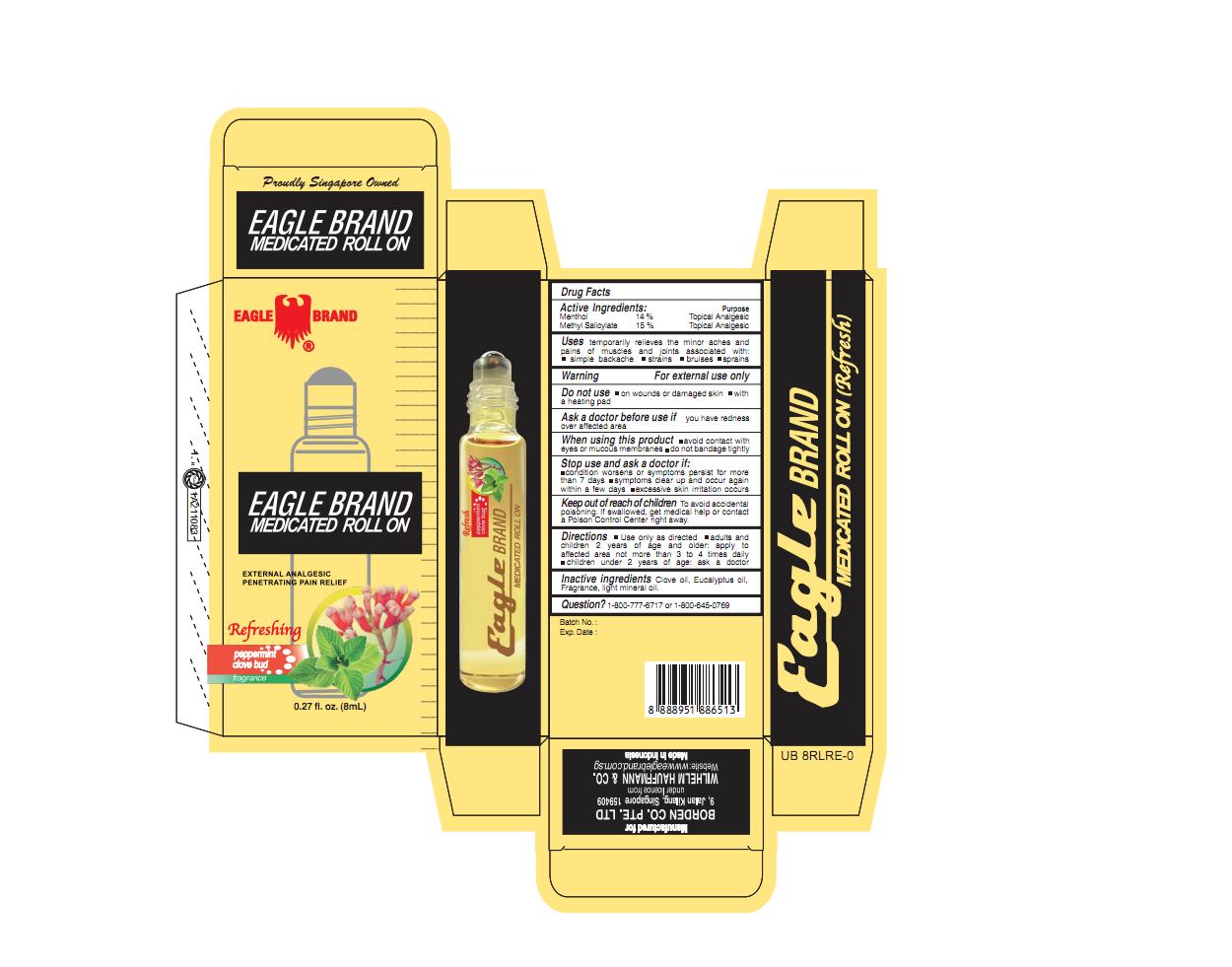 DRUG LABEL: Eagle Medicated Oil
NDC: 60954-005 | Form: OIL
Manufacturer: Eagle Indo Pharma, PT
Category: otc | Type: HUMAN OTC DRUG LABEL
Date: 20241006

ACTIVE INGREDIENTS: METHYL SALICYLATE 15 g/100 mL; MENTHOL 14 g/100 mL
INACTIVE INGREDIENTS: CLOVE OIL; LIGHT MINERAL OIL; EUCALYPTUS OIL

Refreshing External Analgesic OIl

Active Ingredients

Menthol 14%

Methyl Salicylate 15%

Purpose

Topical Analgesic

Topical Analgesic

Uses

temporarily relieves the minor aches and pains of muscles and joints associated with ■simple backache ■strains ■bruises ■ sprains

Warning

For external use only

Do not use

■ on wounds or damaged skin ■ with a heatng pad

Ask a doctor before use if

you have readness over affected area

When using this product

■ avoid contact with eyes or on mucous membranes ■ do not bandage tightly

Stop use and ask a doctor if

■ condition worsens, or symptoms persist for more than 7 days ■ symptoms clear up and occur again within a few days ■ excessive skin irritation occurs

Keep out of reach of children

Keep out of reach of childrenTo avoid accidental poisoning. If swallowed get medical help or contact a Poison Control Center right away

Directions

■ Use only as directed ■ adults and children 2 years of age and older: apply to affected area not more than 3 to 4 times daily. ■ children under 2 years of age: ask a doctor

Inactive Ingredients

clove oil, eucalyptus oil, fragrance, light mineral oil

Question?

1-800-777-6717 or 1-800-645-0769